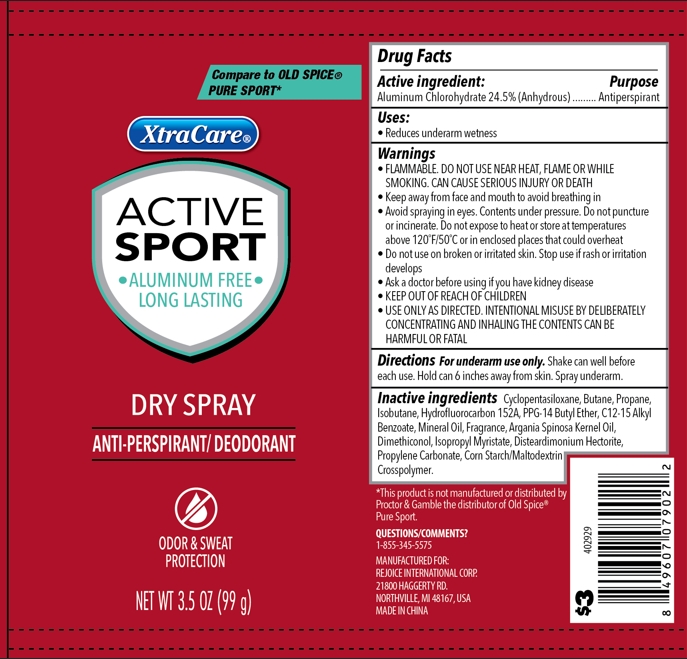 DRUG LABEL: Dry Active Sport 3.5oz
NDC: 57337-177 | Form: SPRAY
Manufacturer: Rejoice International Corp.
Category: otc | Type: HUMAN OTC DRUG LABEL
Date: 20250924

ACTIVE INGREDIENTS: ALUMINUM CHLOROHYDRATE 24.5 g/100 g
INACTIVE INGREDIENTS: C12-15 ALKYL BENZOATE; MINERAL OIL; ARGAN OIL; HYDROFLUOROCARBON 152A; ISOPROPYL MYRISTATE; DIMETHICONOL (2000 CST); STARCH, CORN; PROPANE; ISOBUTANE; BUTANE; DISTEARDIMONIUM HECTORITE; PROPYLENE CARBONATE; CYCLOPENTASILOXANE; PPG-14 BUTYL ETHER

Dry Spray Active Sport 3.5oz

Active ingredient

Aluminum Chlorohydrate 24.5% (Anhydrous)

Purpose

Antiperspirant

Use

Reduces underarm wetness

Warnings

FLAMMABLE. DO NOT USE NEAR HEAT, FLAME OR WHILE SMOKING. CAN CAUSE SERIOUS INJURY OR DEATH.

- USE ONLY AS DIRECTED. INTENTIONAL MISUSE BY DELIBERATELY CONCENTRATING AND INHANDLING THE CONTENTS CAN BE HARMFUL OR FATAL.

When using

- Keep away from face and mouth to avoid breathing in
- Avoid spraying in eyes. Contents under pressure. Do not punture or incinerate. Do not expose to heat or store at temperatures above 120 F/50 C or in enclosed places that could overheat

Do not use on broken or irritated skin.

Stop use

Stop use if rash or irritation develops

Ask a doctor before using if you have kidney disease

KEEP OUT OF REACH OF CHILDREN

Directions

For underarm use only. Shake can well before each use. Hold can 6 inches away from skin. Spray underarm.

Inactive ingredients

Cyclopentasiloxane

Butane

Propane

Isobutane

Hydrofluorocarbon 152A

PPG-14 Butyl Ether

C12-15 Alkyl Benzoate

Mineral Oil

Fragrance

Argania Spinosa Kernel Oil

Dimethiconol

Isopropyl Myristate

Disteardimonium Hectorite

Propylene Carbonate

Corn Starch/Maltodextrin Crosspolymer